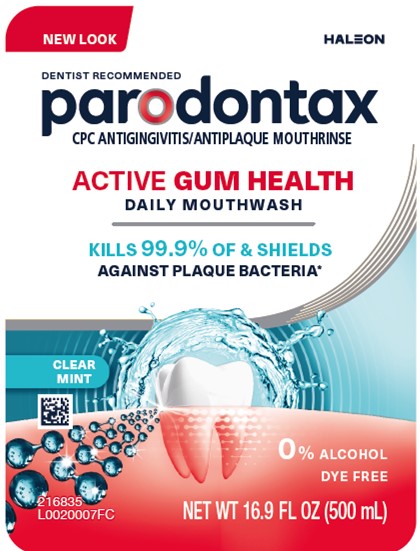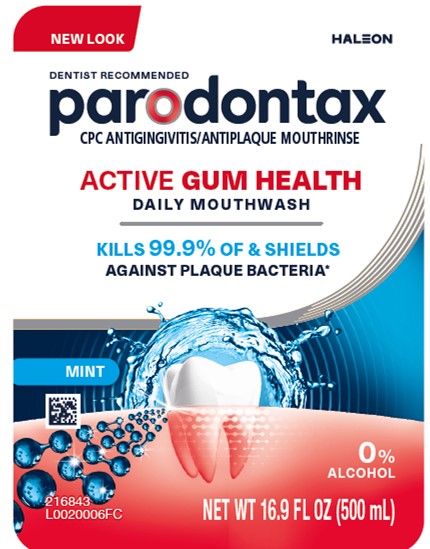 DRUG LABEL: Parodontax

NDC: 0135-0651 | Form: MOUTHWASH
Manufacturer: Haleon US Holdings LLC
Category: otc | Type: HUMAN OTC DRUG LABEL
Date: 20250508

ACTIVE INGREDIENTS: CETYLPYRIDINIUM CHLORIDE 70 mg/1 mL
INACTIVE INGREDIENTS: WATER; GLYCERIN; POLOXAMER 188; SACCHARIN SODIUM; PROPYLENE GLYCOL; SODIUM BENZOATE; SUCRALOSE; 2,3'-IMINODI-BENZOIC ACID; FD&C BLUE NO. 1

Drug Facts

Active ingredient

Cetylpyridinium chloride 0.07% w/w

Purpose

Antigingivitis, Antiplaque

Useshelps prevent and reduce plaque that leads to

- gingivitis, an early form of gum disease
- bleeding gums

Warnings

Stop use and ask a dentist if

- irritation occurs
- gingivitis, bleeding, or redness persists for more than 2 weeks
- you have painful or swollen gums, pus from the gum line, loose teeth, or increasing spacing between the teeth. These may be signs or symptoms of periodontitis, a serious form of gum disease.

Keep out of reach of children under 6 years of age.

If more than used for rinsing is accidentally swallowed, get medical help or contact a Poison Control Center right away.

Directions

- adults and children 6 years of age and older:measure twice up to 10 milliliters mark inside of cap. Vigorously swish 20 milliliters of the rinse between your teeth twice a day for 30 seconds and then spit out. Do not swallow the rinse. Do not rinse with water. Do not drink from the bottle.
- children 6 years to under 12 years of age:supervise use
- children under 6 years of age:do not use

Other information

- this rinse is not intended to replace brushing or flossing
- may cause staining
- Do not store above 25°C or 77°F

Inactive ingredients (Mint)

Water, glycerin, flavor, poloxamer 188, sodium saccharin, propylene glycol, sodium benzoate, sucralose, benzoic acid, blue 1

Inactive Ingredients (Clear Mint)

Water, glycerin, flavor, poloxamer 188, sodium saccharin, propylene glycol, sodium benzoate, sucralose, benzoic acid

Questions or comments?

1-866-844-2797

Additional Information

parodontax

ACTIVE GUMHEALTH

Clinically proven ingredient to protect against gum problems

ALWAYS FOLLOW THE LABEL

Do not use if printed safety seal around cap is broken or missing.

*Kills plaque bacteria associated with gingivitis in a laboratory test

Distributed by: Haleon, Warren, NJ 07059

Trademarks owned or licensed by Haleon.

©2025 Haleon or Licensor.

Proudly made in the USA with US & globally sourced ingredients. Active made in India.

BOTTLE
RECYCLE

CAP
CHECK LOCALLY†

†Recycling facilities for this product may not exist in your area. Cap film not recyclable.

Principal Display Panel

NEW LOOK

HALEON

DENTIST RECOMMENDED

parodontax

CPC ANTIGINGIVITIS/ANTIPLAQUE MOUTHRINSE

ACTIVE GUMHEALTH
DAILY MOUTHWASH

KILLS 99.9% OF & SHIELDS
AGAINST PLAQUEBACTERIA*

MINT

0% ALCOHOL

NET WT 16.9 FL OZ (500 mL)

216843: Front Label

216846: Back Label

Principal Display Panel

NEW LOOK

HALEON

DENTIST RECOMMENDED

parodontax

CPC ANTIGINGIVITIS/ANTIPLAQUE MOUTHRINSE

ACTIVE GUMHEALTH

DAILY MOUTHWASH

KILLS 99.9% OF & SHIELDS
AGAINST PLAQUEBACTERIA*

CLEAR MINT

0% ALCOHOL

DYE FREE

NET WT 16.9 FL OZ (500 mL)

216835: Front Label

216836: Back Label